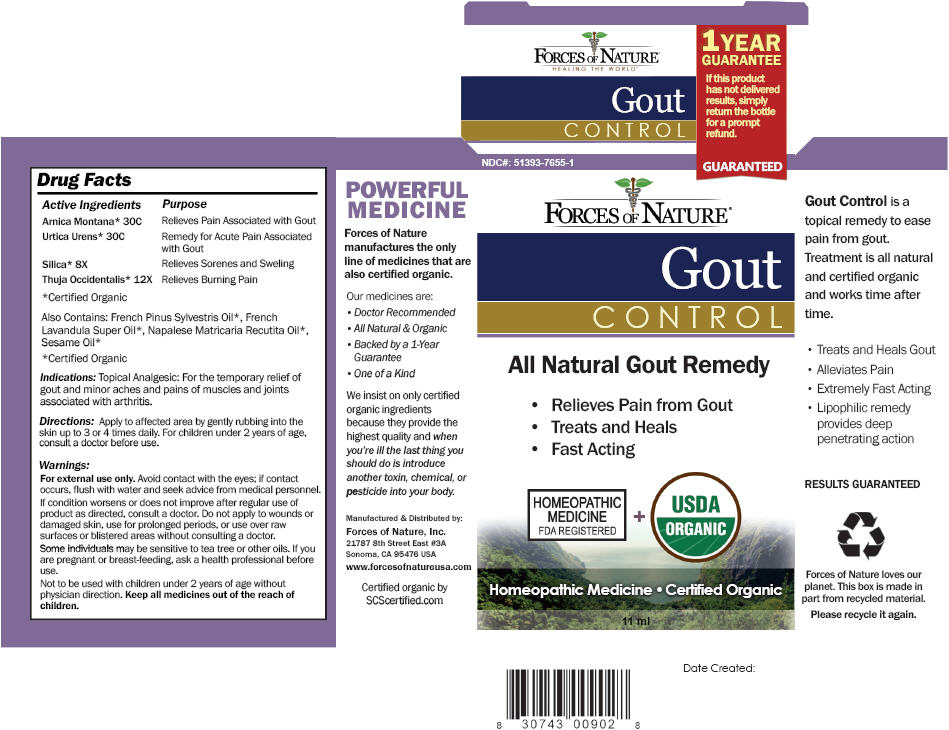 DRUG LABEL: Gout Control
NDC: 51393-7655 | Form: SOLUTION/ DROPS
Manufacturer: Forces of Nature
Category: homeopathic | Type: HUMAN OTC DRUG LABEL
Date: 20120103

ACTIVE INGREDIENTS: Arnica Montana 30 [hp_C]/100 mL; Urtica Urens 30 [hp_C]/100 mL; Silicon Dioxide 8 [hp_X]/1000 mL; Thuja Occidentalis Root 12 [hp_X]/1000 mL
INACTIVE INGREDIENTS: Pine Needle Oil (Pinus Sylvestris); Lavandin Oil; Matricaria Chamomilla Flowering Top Oil; Sesame Oil

FORCES OF NATURE®
Gout
CONTROL

Drug Facts

ACTIVE INGREDIENT

Active Ingredients | Purpose
Arnica Montana [Certified Organic] 30C | Relieves Pain Associated with Gout
Urtica Urens 30C | Remedy for Acute Pain Associated with Gout
Silica 8X | Relieves Sorenes and Sweling
Thuja Occidentalis 12X | Relieves Burning Pain

Also Contains

French Pinus Sylvestris Oil [Certified Organic] , French Lavandula Super Oil, Napalese Matricaria Recutita Oil, Sesame Oil

Indications

Topical Analgesic: For the temporary relief of gout and minor aches and pains of muscles and joints associated with arthritis.

Directions

Apply to affected area by gently rubbing into the skin up to 3 or 4 times daily. For children under 2 years of age, consult a doctor before use.

Warnings

For external use only.

WHEN USING

Avoid contact with the eyes; if contact occurs, flush with water and seek advice from medical personnel.

ASK DOCTOR

If condition worsens or does not improve after regular use of product as directed, consult a doctor. Do not apply to wounds or damaged skin, use for prolonged periods, or use over raw surfaces or blistered areas without consulting a doctor.

Some individuals may be sensitive to tea tree or other oils.

PREGNANCY OR BREAST FEEDING

If you are pregnant or breast-feeding, ask a health professional before use.

DO NOT USE

Not to be used with children under 2 years of age without physician direction.

KEEP OUT OF REACH OF CHILDREN

Keep all medicines out of the reach of children.

Manufactured & Distributed by:

Forces of Nature, Inc.
21787 8th Street East #3A
Sonoma, CA 95476 USA

PRINCIPAL DISPLAY PANEL - 11 ml Bottle Carton

NDC#: 51393-7655-1

GUARANTEED

FORCES OF NATURE®

Gout
CONTROL

All Natural Gout Remedy

- Relieves Pain from Gout
- Treats and Heals
- Fast Acting

HOMEOPATHIC
MEDICINE
FDA REGISTERED
+
USDA
ORGANIC

Homeopathic Medicine • Certified Organic

11 ml